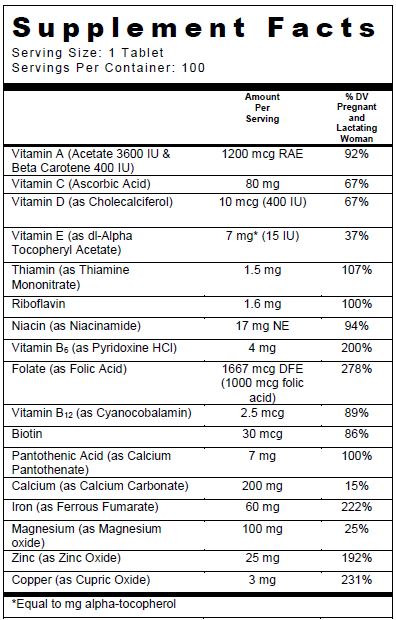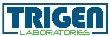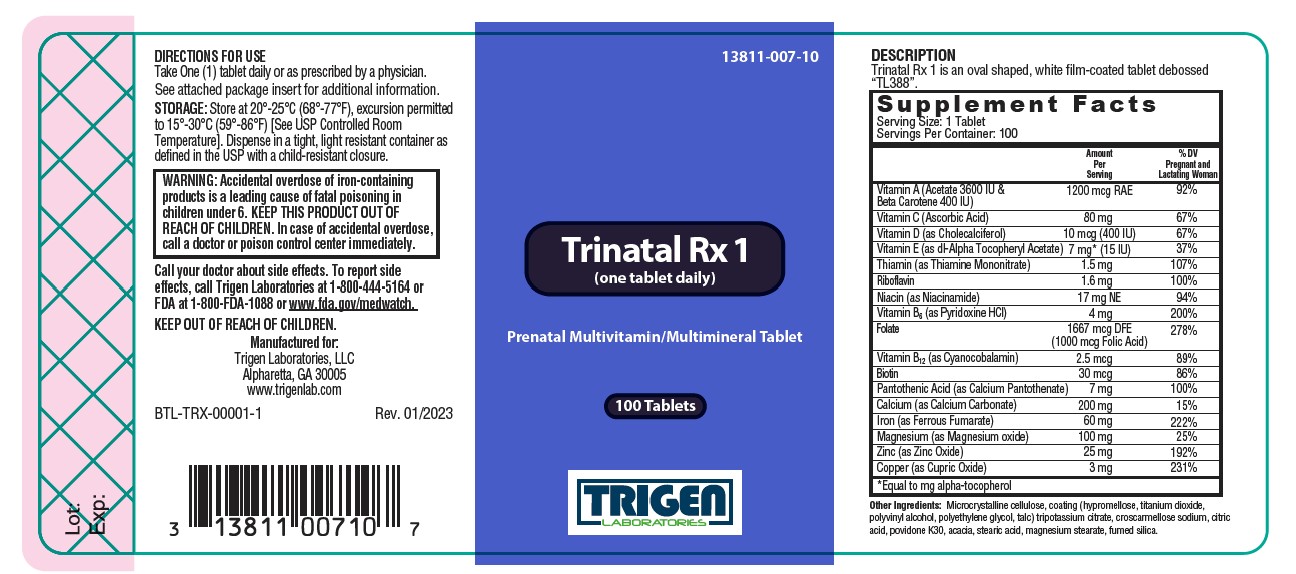 DRUG LABEL: Trinatal Rx 1
NDC: 13811-007 | Form: TABLET, FILM COATED
Manufacturer: Trigen Laboratories, LLC
Category: other | Type: DIETARY SUPPLEMENT
Date: 20230131

ACTIVE INGREDIENTS: acetate ion 3600 [iU]/1 1; BETA CAROTENE 400 [iU]/1 1; cholecalciferol 400 [iU]/1 1; .alpha.-tocopherol acetate, dl- 15 [iU]/1 1; ascorbic acid 80 mg/1 1; folic acid 1 mg/1 1; thiamine mononitrate 1.5 mg/1 1; riboflavin 1.6 mg/1 1; niacinamide 17 mg/1 1; pyridoxine Hydrochloride 4 mg/1 1; cyanocobalamin 2.5 ug/1 1; biotin 30 ug/1 1; calcium pantothenate 7 mg/1 1; calcium carbonate 200 mg/1 1; magnesium oxide 100 mg/1 1; ferrous fumarate 60 mg/1 1; cupric oxide 3 mg/1 1; zinc oxide 25 mg/1 1
INACTIVE INGREDIENTS: cellulose, microcrystalline; hypromelloses; titanium dioxide; POLYVINYL ALCOHOL, UNSPECIFIED; POLYETHYLENE GLYCOL, UNSPECIFIED; talc; potassium citrate anhydrous; croscarmellose sodium; citric acid monohydrate; povidone K30; acacia; stearic acid; magnesium stearate; SILICON DIOXIDE

Trinatal Rx 1
Prenatal Multivitamin/Mineral Tablet

SUPPLEMENT FACTS

Other Ingredients: Microcrystalline cellulose, coating (hypromellose, titanium dioxide, polyvinyl alcohol, polyethylene glycol, talc) tripotassium citrate, croscarmellose sodium, citric acid, povidone K30, acacia, stearic acid, magnesium stearate, fumed silica.

Trinatal Rx 1 tablets help assure an adequate intake of the vitamins and minerals listed. Folate supplementation may be recommended for individuals who have higher-than-normal demands for folate such as pregnant women.

CONTRAINDICATIONS

Supplemental vitamins and minerals should not be prescribed for patients with hemochromatosis or Wilson’s disease.

WARNINGS

WARNING: Accidental overdose of iron-containing products is a leading cause of fatal poisoning in children under 6. KEEP THIS PRODUCT OUT OF REACH OF CHILDREN. In case of accidental overdose, call a doctor or poison control center immediately.

PRECAUTIONS

General: Folic acid alone is improper therapy in the treatment of pernicious anemia and other megaloblastic anemias where vitamin B12 is deficient. Folic acid in doses above 0.1 mg daily may obscure pernicious anemia assessment, such that hematologic remission can occur while neurological manifestations remain progressive. Pernicious anemia should be excluded before using this product since folic acid may mask the symptoms of pernicious anemia. The calcium content should be considered before prescribing for patients with history of kidney stones. Do not exceed the recommended dose.

Biotin levels higher than the recommended daily allowance may cause interference with some laboratory tests, including cardiovascular diagnostic tests (e.g. troponin) and hormone test, and may lead to incorrect test results. Tell your healthcare provider about all prescription and over-the-counter medicines, vitamins, and dietary supplements that you take, including biotin.

Pediatric Use: Safety and effectiveness in pediatric patients have not been established.

Geriatric Use: Safety and effectiveness in elderly patients have not been established.

DRUG INTERACTIONS

Trinatal Rx 1 is not recommended for and should not be given to patients receiving levodopa because the action of levodopa is antagonized by pyridoxine. There is a possibility of increased bleeding due to pyridoxine interaction with anticoagulants (e.g., Aspirin, Heparin, Clopidogrel).

ADVERSE REACTIONS

Adverse reactions with iron therapy may include constipation, diarrhea, nausea, vomiting, dark stools and abdominal pain. Adverse reactions with iron therapy are usually transient. Allergic sensitization has been reported following both oral and parenteral administration of folic acid. Allergic sensitization has been reported following both oral and parenteral administration of folic acid.

DESCRIPTION

Trinatal Rx 1 is an oval shaped, white film-coated tablet debossed "TL388".

DIRECTIONS FOR USE

Take One (1) tablet daily or as prescribed by a physician.

HOW SUPPLIED

Trinatal Rx 1 is supplied in bottles of 100 tablets.

Product Code: 13811-007-10

STORAGE

Store at 20°-25°C (68°-77°F), excursion permitted to 15°-30°C (59°-86°F) [See USP Controlled Room Temperature]. Dispense in a tight, light resistant container as defined in the USP with a child-resistant closure.

KEEP OUT OF REACH OF CHILDREN.

For use on the order of a healthcare practitioner.

Call your doctor about side effects. To report side effects, call Trigen Laboratories at 1-800-444-5164 or FDA at 1-800-FDA-1088.

PI-TRX-00001-2 Rev. 05/2023

Manufactured for:

Trigen Laboratories, LLC

Alpharetta, GA 30005

PRINCIPAL DISPLAY PANEL - 100 Tablet Bottle Label

13811-007-10

100 Tablets

Trinatal Rx 1
(one tablet daily)

Prenatal Multivitamin/Multimineral Tablet

TRIGEN
LABORATORIES